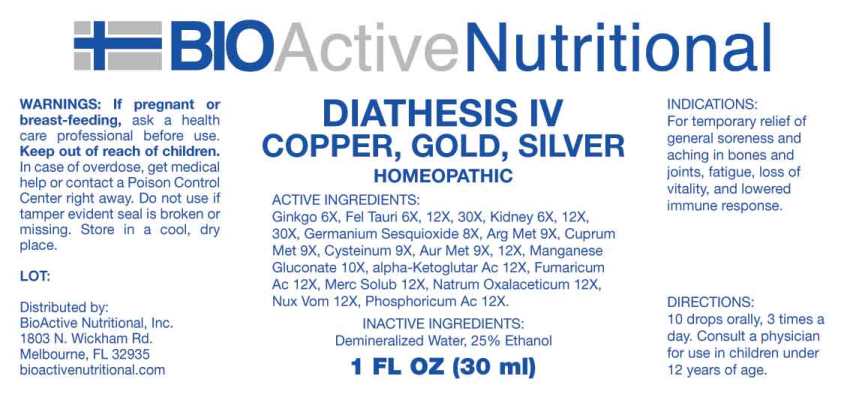 DRUG LABEL: Diathesis
NDC: 43857-0631 | Form: LIQUID
Manufacturer: BioActive Nutritional, Inc.
Category: homeopathic | Type: HUMAN OTC DRUG LABEL
Date: 20230413

ACTIVE INGREDIENTS: GINKGO 6 [hp_X]/1 mL; BOS TAURUS BILE 6 [hp_X]/1 mL; PORK KIDNEY 6 [hp_X]/1 mL; GERMANIUM SESQUIOXIDE 8 [hp_X]/1 mL; SILVER 9 [hp_X]/1 mL; COPPER 9 [hp_X]/1 mL; CYSTEINE 9 [hp_X]/1 mL; GOLD 9 [hp_X]/1 mL; MANGANESE GLUCONATE 10 [hp_X]/1 mL; OXOGLURIC ACID 12 [hp_X]/1 mL; FUMARIC ACID 12 [hp_X]/1 mL; MERCURIUS SOLUBILIS 12 [hp_X]/1 mL; SODIUM DIETHYL OXALACETATE 12 [hp_X]/1 mL; STRYCHNOS NUX-VOMICA SEED 12 [hp_X]/1 mL; PHOSPHORIC ACID 12 [hp_X]/1 mL
INACTIVE INGREDIENTS: WATER; ALCOHOL

DRUG FACTS:

ACTIVE INGREDIENTS:

Ginkgo Biloba 6X, Fel Tauri 6X, 12X, 30X, Kidney 6X, 12X, 30X, Germanium Sesquioxide 8X, Argentum Metallicum 9X, Cuprum Metallicum 9X, Cysteinum 9X, Aurum Metallicum 9X, 12X, Manganese Gluconate 10X, Alpha-Ketoglutaricum Acidum 12X, Fumaricum Acidum 12X, Mercurius Solubilis 12X, Natrum Oxalaceticum 12X, Nux Vomica 12X, Phosphoricum Acidum 12X.

PURPOSE:

For temporary relief of general soreness and aching in bones and joints, fatigue, loss of vitality, and lowered immune response.

WARNINGS:

If pregnant or breast-feeding, ask a health care professional before use.

Keep out of reach of children. In case of overdose, get medical help or contact a Poison Control Center right away.

Do not use if tamper evident seal is broken or missing. Store in cool, dry place.

KEEP OUT OF REACH OF CHILDREN:

In case of overdose, get medical help or contact a Poison Control Center right away.

DIRECTIONS:

10 drops orally, 3 times a day. Consult a physician for use in children under 12 years of age.

INDICATIONS:

For temporary relief of general soreness and aching in bones and joints, fatigue, loss of vitality, and lowered immune response.

INACTIVE INGREDIENTS:

Demineralized Water, 25% Ethanol

QUESTIONS:

Distributed by:
BioActive Nutritional, Inc.
1803 N. Wickham Rd.
Melbourne, FL 32935
bioactivenutritional.com

PACKAGE LABEL DISPLAY:

BIOActive Nutritional

DIATHESIS IV

COPPER, GOLD, SILVER

HOMEOPATHIC

1 FL OZ (30 ml)